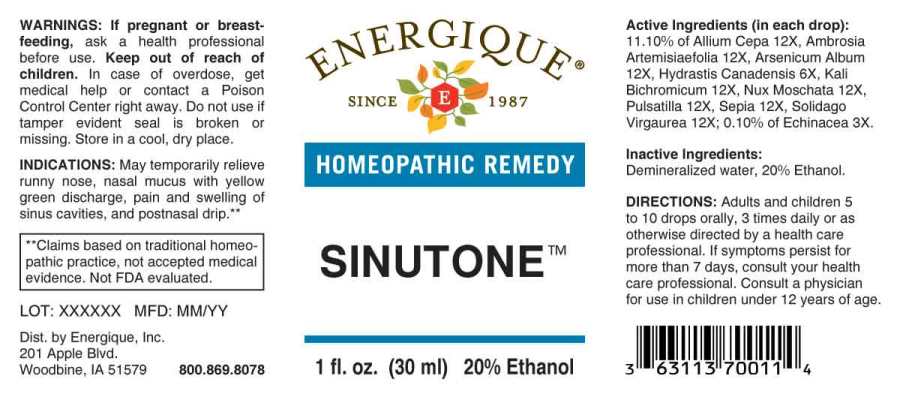 DRUG LABEL: Sinutone
NDC: 44911-0515 | Form: LIQUID
Manufacturer: Energique, Inc.
Category: homeopathic | Type: HUMAN OTC DRUG LABEL
Date: 20240419

ACTIVE INGREDIENTS: ECHINACEA ANGUSTIFOLIA WHOLE 3 [hp_X]/1 mL; GOLDENSEAL 6 [hp_X]/1 mL; ONION 12 [hp_X]/1 mL; AMBROSIA ARTEMISIIFOLIA WHOLE 12 [hp_X]/1 mL; ARSENIC TRIOXIDE 12 [hp_X]/1 mL; POTASSIUM DICHROMATE 12 [hp_X]/1 mL; NUTMEG 12 [hp_X]/1 mL; PULSATILLA PRATENSIS WHOLE 12 [hp_X]/1 mL; SEPIA OFFICINALIS JUICE 12 [hp_X]/1 mL; SOLIDAGO VIRGAUREA FLOWERING TOP 12 [hp_X]/1 mL
INACTIVE INGREDIENTS: WATER; ALCOHOL

DRUG FACTS:

ACTIVE INGREDIENTS:

(in each drop): 11.10% of Allium Cepa 12X, Ambrosia Artemisiaefolia 12X, Arsenicum Album 12X, Hydrastis Canadensis 6X, Kali Bichromicum 12X, Nux Moschata 12X, Pulsatilla (Pratensis) 12X, Sepia 12X, Solidago Virgaurea 12X; 0.10% of Echinacea (Angustifolia) 3X.

INDICATIONS:

May temporarily relieve allergic rhinitis with runny nose, nasal mucus with yellow green discharge, pain and swelling of sinus cavities, and postnasal drip.**

**Claims based on traditional homeopathic practice, not accepted medical evidence. Not FDA evaluated.

WARNINGS:

If pregnant or breast-feeding, ask a health professional before use.

Keep out of reach of children. In case of overdose, get medical help or contact a Poison Control Center right away.

Do not use if tamper evident seal is broken or missing. Store in a cool, dry place.

Keep out of reach of children. In case of overdose, get medical help or contact a Poison Control Center right away.

DIRECTIONS:

Adults and children 5 to 10 drops orally, 3 times daily or as otherwise directed by a health care professional. If symptoms persist for more than 7 days, consult your health care professional. Consult a physician for use in children under 12 years of age.

INDICATIONS:

May temporarily relieve allergic rhinitis with runny nose, nasal mucus with yellow green discharge, pain and swelling of sinus cavities, and postnasal drip.**

**Claims based on traditional homeopathic practice, not accepted medical evidence. Not FDA evaluated.

INACTIVE INGREDIENTS:

Demineralized water, 20% Ethanol.

QUESTIONS:

Dist. by Energique, Inc.

201 Apple Blvd.
Woodbine, IA 51579 800-869-8078

PACKAGE LABEL DISPLAY:

ENERGIQUE

SINCE 1987

HOMEOPATHIC REMEDY

SINUTONE

1 fl. oz. (30 ml)